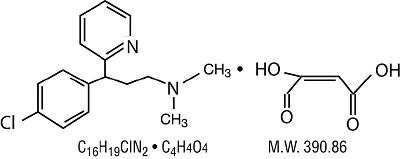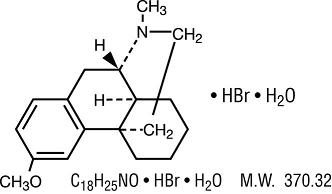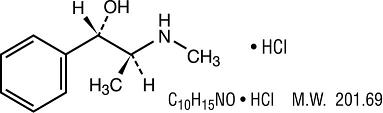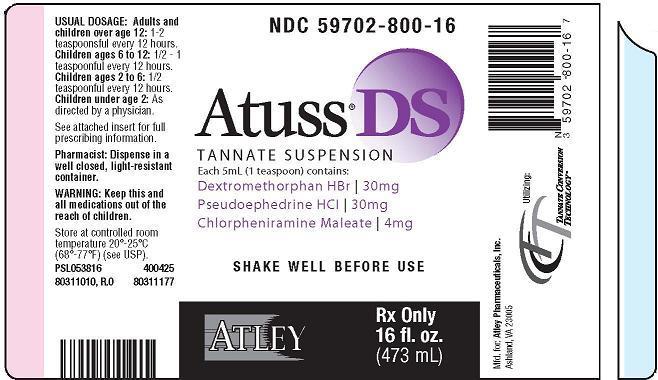 DRUG LABEL: Atuss DS Tannate Suspension
NDC: 59702-800 | Form: SUSPENSION
Manufacturer: Atley Pharmaceuticals, Inc.
Category: prescription | Type: HUMAN PRESCRIPTION DRUG LABEL
Date: 20100222

ACTIVE INGREDIENTS: Dextromethorphan Hydrobromide 30 mg/5 mL; Pseudoephedrine Hydrochloride 30 mg/5 mL; Chlorpheniramine Maleate 4 mg/5 mL

Atuss® DS Tannate Suspension Antitussive Decongestant Antihistamine Rx Only PIN 400425 ISS 10/09

DESCRIPTION

Each teaspoonful (5 mL) of Atuss® DS Tannate Suspension contains:

Dextromethorphan Hydrobromide . . . . . . . . . . . . . . . . . . . . . . . . . . . . . . . . 30 mg

Pseudoephedrine Hydrochloride . . . . . . . . . . . . . . . . . . . . . . . . . . . . . . . . . 30 mg

Chlorpheniramine Maleate . . . . . . . . . . . . . . . . . . . . . . . . . . . . . . . . . . . . . . 4 mg

Atuss® DS Tannate Suspension is used for oral administration only.

Atuss® DS Tannate Suspension contains the following inactive ingredients: Acesulfame K, Artificial Bubblegum Flavor, Artificial Grape Flavor, Aspartame, Bitter Mask, Citric Acid, FDC Blue #1, FDC Red #40, Glycerin, Hydrochloric Acid, Methylparaben, Magnesium Aluminometasilicate, Purified Water, Sodium Citrate Dihydrate, Sodium Hydroxide, Sucralose, Xanthan Gum. Plus tannic acid yielding a tannate suspension.

Dextromethorphan Hydrobromide:
3-Methoxy-17-methyl-9α, 13α, 14α-morphinan.

Pseudoephedrine Hydrochloride:
[S(R*, R*)]- α -[1-(methylamino)ethyl] benzenemethanol hydrochloride.

Chlorpheniramine Maleate:
2-[p-chloro- α -[2-(dimethylamino) ethyl]-benzyl] pyridine.

CLINICAL PHARMACOLOGY

Dextromethorphan is an antitussive agent which, unlike the isomeric levorphanol, has no analgesic or addictive properties. The drug acts centrally and elevates the threshold for coughing. It is about equal to codeine in depressing the cough reflex. In therapeutic dosage, dextromethorphan does not inhibit ciliary activity. Dextromethorphan is rapidly absorbed from the gastrointestinal tract, metabolized by the liver and excreted primarily in the urine.

Pseudoephedrine is an α-adrenergic receptor antagonist (sympathomimetic) which produces vasoconstriction by stimulating α-receptors within the mucosa of the respiratory tract. Clinically, pseudoephedrine shrinks swollen mucous membranes, reduces tissue hyperemia, edema, and nasal congestion, and increases nasal airway patency. The vasoconstriction action of pseudoephedrine is similar to that of ephedrine. In the usual dose it has minimal vasopressor effects. Pseudoephedrine is rapidly and almost completely absorbed from the gastrointestinal tract. Acidic urine is associated with faster elimination of the drug. The drug is distributed to body tissues and fluids, including the fetal tissue, breast milk and the central nervous system (CNS).

Chlorpheniramine is an alkylamine-type antihistamine. The antihistamine in Atuss® DS Tannate Suspension acts by competing with histamine for H1 histamine receptor sites, thereby preventing the action of histamine on the cell. Clinically, chlorpheniramine suppresses the histamine-mediated symptoms of allergic rhinitis, relieving sneezing, rhinorrhea, and itching of the eyes, nose, and throat.

INDICATIONS

Atuss® DS Tannate Suspension is indicated for temporary relief of nasal congestion and cough associated with respiratory tract infections and related conditions such as sinusitis, pharyngitis, bronchitis and asthma when these conditions are complicated by tenacious mucus and/or mucous plugs and congestion. Atuss® DS Tannate Suspension is effective in a productive as well as a nonproductive cough, but is of particular value in a dry nonproductive cough which tends to injure the mucous membrane of the air passages.

CONTRAINDICATIONS

Atuss® DS Tannate Suspension is contraindicated in patients with hypersensitivity to chlorpheniramine, dextromethorphan, or with hypersensitivity or idiosyncrasy to sympathomimetic amines which may be manifested by insomnia, dizziness, weakness, tremor or arrhythmias. Sympathomimetic amines are contraindicated in patients with severe hypertension, severe coronary artery disease, and patients that are now taking a prescription monoamine oxidase inhibitor (MAOI) (certain drugs for depression, psychiatric, or emotional conditions, or Parkinson’s disease), or for two weeks after stopping the MAOI drug. This product is contraindicated in woman who are pregnant or nursing.

WARNINGS

Do not take this product for persistent or chronic cough such as occurs with smoking, asthma, chronic bronchitis, or emphysema, or where cough is accompanied by excessive phlegm (mucus) unless directed by a doctor. Sympathomimetic amines should be used with caution in patients with hypertension, ischemic heart disease, diabetes mellitus, increased intraocular pressure, hyperthyroidism, or prostatic hypertrophy. Sympathomimetics may produce central nervous system stimulation with convulsions or cardiovascular collapse with accompanying hypotension. Nervousness, dizziness or sleeplessness may occur at higher doses.

Hypertensive crises can occur with concurrent use of pseudoephedrine and MAOI, indomethacin, or with beta blockers and methyldopa. If a hypertensive crisis occurs, these drugs should be discontinued immediately and therapy to lower blood pressure should be instituted. Fever should be managed by means of external cooling. Do not exceed recommended dosage.

PRECAUTIONS

General:

Before prescribing medication to suppress or modify cough, it is important that the underlying cause of cough is identified, that modification of cough does not increase the risk of clinical or physiologic complications, and that appropriate therapy for the primary disease is instituted. Check with physician if cough persists after medication has been used for seven days or if high fever, skin rash, or continued headache, or sore throat is present with cough. Caution should be exercised in patients with high blood pressure, heart disease, diabetes mellitus, or thyroid disease. Dextromethorphan should be used with caution in sedated or debilitated patients, and in patients confined to the supine position. Administration of dextromethorphan may be accompanied by histamine release and should be used with caution in atopic children. The antihistamine in Atuss® DS Tannate Suspension may exhibit additive effects with CNS depressants, including alcohol.

Phenylketonurics:

Contains Phenylalanine 25.25 mg. per 5 mL.

Information for Patients:

Patient consultation should include the following information regarding proper use of Atuss® DS Tannate Suspension:

- Atuss® DS Tannate Suspension may be taken with food to minimize gastric irritation.
- Do not take MAOI while taking Atuss® DS Tannate Suspension.
- Keep all medications out of the reach of children. In case of accidental overdose, seek professional assistance or contact a poison control center immediately.
- Antihistamines may impair mental and physical abilities required for the performance of potentially hazardous tasks, such as driving a vehicle or operating machinery.

Drug Interactions:

- MAOI and tricyclic antidepressants may prolong and intensify the anticholinergic (drying) effects of antihistamines.
- Beta-adrenergic blockers and MAOI may potentiate the pressor effect of pseudoephedrine.
- Concurrent use of digitalis glycosides may increase the possibility of cardiac arrhythmias.
- Sympathomimetics may reduce the hypotensive effects of guanethidine, mecamylamine, methyldopa, reserpine and veratrum alkaloids.
- Concurrent use of tricyclic antidepressants may antagonize the effects of pseudoephedrine.
- Concomitant use of antihistamines with alcohol, tricyclic antidepressants, barbiturates and other CNS depressants may have an additive effect.

Laboratory Test Interactions:

The in vitro addition of pseudoephedrine to sera containing the cardiac isoenzyme MB of serum creatine phosphokinase progressively inhibits the activity of the enzyme. The inhibition becomes complete over six hours.

Carcinogenesis, Mutagenesis, Impairment of Fertility:

No data is available on the long-term potential of the components of Atuss® DS Tannate Suspension for carcinogenesis, mutagenesis or impairment of fertility in animals or humans.

Pregnancy: Category C:

Animal reproduction studies have not been conducted with Atuss® DS Tannate Suspension. It is also not known if Atuss® DS Tannate Suspension can cause fetal harm when administered to a pregnant woman or can affect reproduction capacity.

Nursing Mothers:

Pseudoephedrine is excreted in breast milk. Use of Atuss® DS Tannate Suspension by nursing mothers is not recommended because of the higher-than-usual risk for infants from sympathomimetic amines.

Pediatric Use:

Safety and effectiveness of Atuss® DS Tannate Suspension in pediatric patients under the age of two years have not been established. Pseudoephedrine may be more likely to cause side effects in infants, especially newborn and premature infants, than in older children and adults. No age specific problems related to dextromethorphan or chlorpheniramine have been documented in the pediatric population to date. Demonstrate safe use of a short-acting sympathomimetic amine before use of a sustained-action formulation in pediatric patients.

Geriatric Use: (Ages 65 and older)

Geriatric patients taking sympathomimetics may be more likely to experience confusion, hallucinations, seizures, and central nervous system depression. Geriatric patients may also be more sensitive to the effects, especially to the vasopressor effects, of sympathomimetic amines. Demonstrate safe use of a short-acting sympathomimetic formulation before use of a sustained-action formulation in elderly patients.

ADVERSE REACTIONS

Pseudoephedrine may cause mild central nervous system stimulation, especially in those patients who are hypersensitive to sympathomimetic drugs. Nervousness, excitability, restlessness, dizziness, weakness and insomnia may also occur. Headache and drowsiness have also been reported. Large doses may cause lightheadedness, nausea and/or vomiting. Sympathomimetics have been associated with certain untoward reactions including fear, anxiety, nervousness, restlessness, tremor, weakness, pallor, respiratory difficulty, dysuria, insomnia, hallucinations, convulsions, CNS depression, arrhythmias, and cardiovascular collapse with hypotension. Adverse effects associated with dextromethorphan are generally infrequent and mild. Products containing dextromethorphan have been associated with nausea, dizziness, fatigue, gastrointestinal disturbances, and skin eruptions.

Chlorpheniramine may cause slight to moderate drowsiness and is the most frequent side effect. Other possible side effects of antihistamines include:

General: Urticaria, drug rash, anaphylactic shock, photosensitivity, excessive perspiration, chills, dryness of mouth, nose and throat;

Cardiovascular: Hypotension, headache, palpitation, tachycardia, extra systoles;

Hematological: Hemolytic anemia, thrombocytopenia, agranulocytosis;

CNS: Sedation, dizziness, disturbed coordination, fatigue, confusion, restlessness, excitation, nervousness, tremor, irritability, insomnia, euphoria, paresthesia, blurred vision, diplopia, vertigo, tinnitus, hysteria, neuritis, convulsion;

Gastrointestinal: Epigastric distress, anorexia, nausea, vomiting, diarrhea, constipation;

Genitourinary: Urinary frequency, difficult urination, urinary retention, early menses;

Respiratory: Thickening of bronchial secretions, tightness of chest, wheezing and nasal stuffiness.

DRUG ABUSE AND DEPENDENCE:

Pseudoephedrine, like other CNS stimulants, has been abused. At high doses, subjects commonly experience an elevation of mood, a sense of increased energy and alertness, and decreased appetite. Some individuals become anxious, irritable, and loquacious. In addition to the marked euphoria, the user experiences a sense of markedly enhanced physical strength and mental capacity. With continued use, tolerance develops, the user increases the dose and toxic signs and symptoms appear. Depression may follow rapid withdrawal. Narcotic antitussives and stimulants, such as pseudoephedrine, are banned and tested for by the U.S. Olympic Committee (USOC) and the National Collegiate Athletic Association (NCAA).

OVERDOSAGE:

Overdosage with pseudoephedrine may manifest itself as excessive CNS stimulation resulting in excitement, tremor, restlessness and insomnia. Other effects may include tachycardia, hypertension, pallor, mydriasis, hyperglycemia and urinary retention. Severe overdosage may cause tachypnea or hyperpnea, hallucinations, convulsions or delirium, but in some individuals there may be CNS depression with somnolence, stupor or respiratory depression. Arrhythmias (including ventricular fibrillation) may lead to hypotension and circulatory collapse. Severe hypokalemia can occur, probably due to a compartmental shift rather than a depletion of potassium. No organ damage or significant metabolic derangement is associated with pseudoephedrine overdosage. Overdose with dextromethorphan include CNS effects as most prevalent, such as psychosis, hallucinations, mania, seizures, ataxia, dizziness, and psychological dependence. Urinary retention and tachycardia have also been reported. Very high doses may lead to respiratory depression coma/unconsciousness, and cyanosis.Manifestations of antihistamine overdosage may vary from CNS depression (sedation, apnea, cardiovascular collapse) to stimulation (insomnia, hallucinations, tremors or convulsions). Other signs and symptoms may be dizziness, tinnitus, ataxia, blurred vision, and hypotension. Stimulation is particularly likely in children, as are atropine-like signs and symptoms (dry mouth; fixed, dilated pupils; flushing; hyperthermia and gastrointestinal symptoms).

Treatment:

In the event of overdosage, emergency treatment should be started immediately. Since the action of long-acting products may continue for as long as 18 hours, treatment of overdosage should be directed toward reducing further absorption and supporting the patient for at least that length of time. Gastric emptying (Syrup of Ipecac) and/or lavage is recommended as soon as possible after ingestion, even if the patient has vomited spontaneously. Either isotonic or half-isotonic saline may be used for lavage. Administration of an activated charcoal slurry is beneficial after lavage and/or emesis if less than four hours have passed since ingestion. Saline cathartics, such as Milk of Magnesia, are useful for hastening the evacuation of unreleased medication. Adrenergic receptor blocking agents are antidotes to pseudoephedrine. In practice, the most useful is the beta-blocker propanolol, which is indicated when there are signs of cardiac toxicity. In severe cases of overdosage, it is essential to monitor both the heart (by electrocardiograph) and plasma electrolytes, and to give intravenous potassium as indicated.

Vasopressors may be used to treat hypotension. Excessive CNS stimulation may be counteracted with parenteral diazepam. Stimulants should not be used. Hyperpyrexia, especially in children, may require treatment with tepid water sponge baths or a hyperthermic blanket. Apnea is treated with ventilatory support.

DOSAGE AND ADMINISTRATION:

Adults and children over age 12: 1–2 teaspoonsful every 12 hours. Children ages 6 to 12: 1/2 – 1 teaspoonful every 12 hours. Children ages 2 to 6: 1/2 teaspoonful every 12 hours. Children under age 2: As directed by a physician.

Shake well before use.

Note: The hydrobromide salt of dextromethorphan, the hydrochloride salt of pseudoephedrine, and the maleate salt of chlorpheniramine are provided in a tannate suspension by means of the TCT manufacturing process. This yields a corresponding 60 mg of dextromethorphan tannate, 60 mg of pseudoephedrine tannate, and 8 mg of chlorpheniramine tannate.

HOW SUPPLIED:

Atuss® DS Tannate Suspension is a grape bubblegum flavored suspension. Available in 16 fl. oz. (473 mL) NDC 59702-800-16 and 1/2 fl. oz. (15 mL) NDC 59702-800-15.

Storage:

Dispense in a well closed, light-resistant container. Store at controlled room temperature, 20°–25°C (68°–77°F).

WARNINGS:

KEEP THIS AND ALL MEDICATIONS OUT OF THE REACH OF CHILDREN. IN CASE OF ACCIDENTAL OVERDOSE, SEEK PROFESSIONAL ASSISTANCE OR CONTACT A POISON CONTROL CENTER IMMEDIATELY.

Manufactured for:

Atley Pharmaceuticals, Inc.
Ashland, VA 23005

U.S. Patent's
# 6,869,618
# 7,094,429

PIN 400425
ISS. 10/09
Rx Only

© 2007 Atley Pharmaceuticals, Inc. All Rights Reserved

PACKAGE LABEL

REPRESENTATIVE PACKAGING
See How Supplied section for a complete list of available packages of Atuss® DS Tannate Suspension
NDC 59702-800-16
Atuss® DS
Tannate Suspension
Each 5mL (1 teaspoon) contains:
Dextromethorphan HBr 30mg
Pseudoephedrine HCI 30mg
Chlorpheniramine Maleate 4mg
SHAKE WELL BEFORE USING
ATLEY
Rx Only
16 fl. oz. (473 mL)
USUAL DOSAGE:
Adults and children over age 12: 1-2 teaspoonsful every 12 hours.
Children ages 6 to 12: 1/2 - 1 teaspoonful every 12 hours.
Children ages 2 to 6: 1/2 teaspoonful every 12 hours.
Children under age 2: As directed by a physician.
See attached insert for full prescribing information.
Pharmacist: Dispense in a well closed, light-resistant container.
WARNING: Keep this and all medications out of the reach of children.
Store at controlled room temperature 20°-25°C (68°-77°F) (see USP)
PSL053816
400425
80311010, R.0
80311177
Mfg. for: Atley Pharmaceuticals, Inc.
Ashland, VA 23005
Utilizing: Tannate Conversion Technology